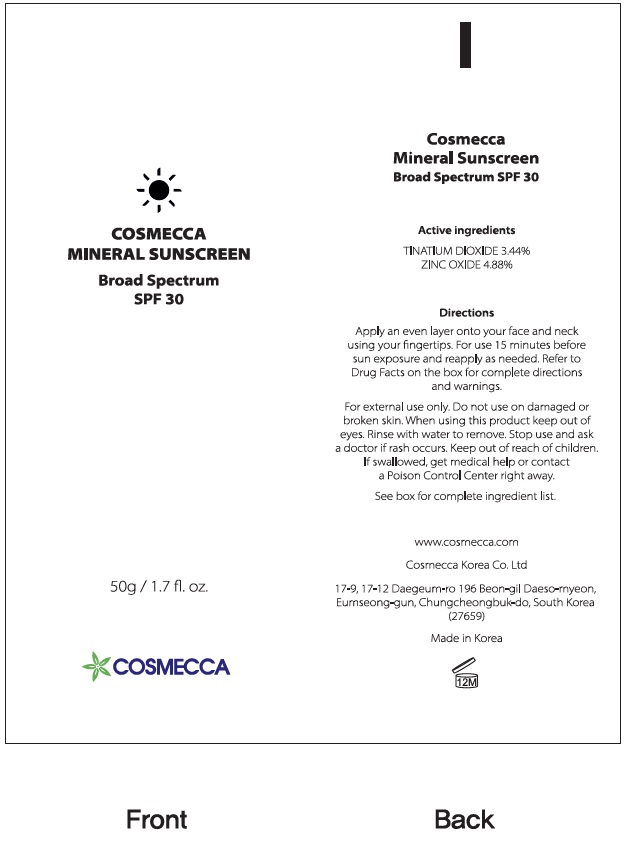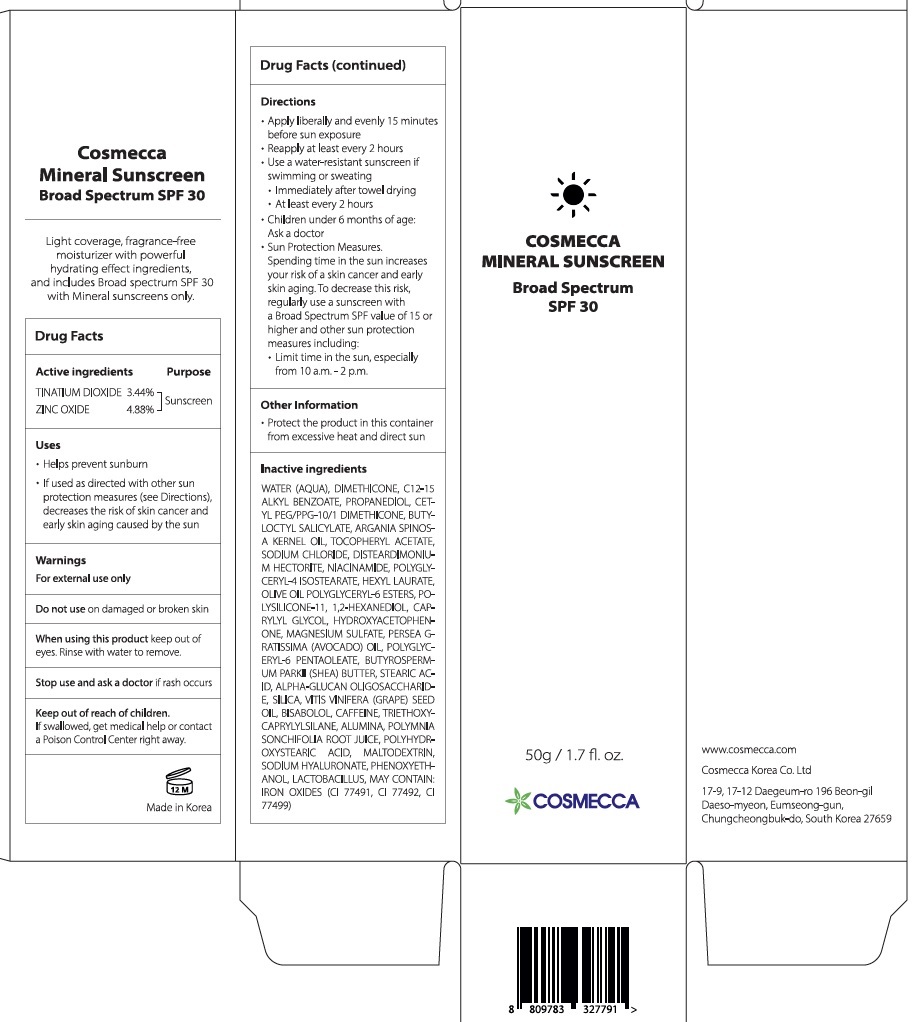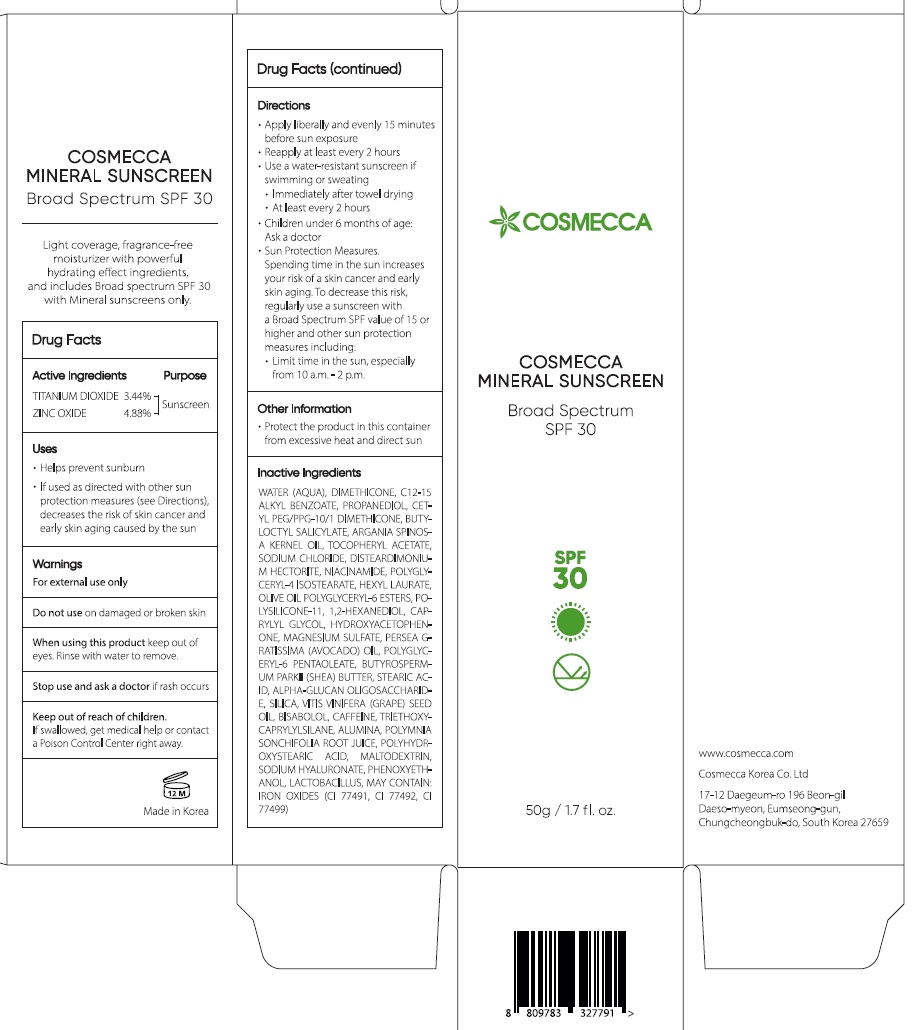 DRUG LABEL: Mineral Sunscreen Broad Spectrum SPF30
NDC: 53727-121 | Form: LOTION
Manufacturer: COSMECCA KOREA CO., LTD
Category: otc | Type: HUMAN OTC DRUG LABEL
Date: 20231212

ACTIVE INGREDIENTS: TITANIUM DIOXIDE 34.4 mg/1 g; ZINC OXIDE 48.8 mg/1 g
INACTIVE INGREDIENTS: LEVOMENOL; CAFFEINE; TRIETHOXYCAPRYLYLSILANE; ALUMINUM OXIDE; SMALLANTHUS SONCHIFOLIUS ROOT JUICE; MALTODEXTRIN; HYALURONATE SODIUM; PHENOXYETHANOL; WATER; DIMETHICONE; ALKYL (C12-15) BENZOATE; PROPANEDIOL; BUTYLOCTYL SALICYLATE; ARGAN OIL; .ALPHA.-TOCOPHEROL ACETATE; SODIUM CHLORIDE; DISTEARDIMONIUM HECTORITE; NIACINAMIDE; POLYGLYCERYL-4 ISOSTEARATE; HEXYL LAURATE; OLIVE OIL POLYGLYCERYL-6 ESTERS; DIMETHICONE/VINYL DIMETHICONE CROSSPOLYMER (SOFT PARTICLE); 1,2-HEXANEDIOL; CAPRYLYL GLYCOL; HYDROXYACETOPHENONE; MAGNESIUM SULFATE, UNSPECIFIED FORM; AVOCADO OIL; POLYGLYCERYL-10 PENTAOLEATE; SHEA BUTTER; STEARIC ACID; .ALPHA.-GLUCAN OLIGOSACCHARIDE; SILICON DIOXIDE; GRAPE SEED OIL

Mineral Sunscreen Broad Spectrum SPF30

Active Ingredients

TITANIUM DIOXIDE 3.44%

ZINC OXIDE 4.88%

PURPOSE

Sunscreen

Uses

- Helps prevent sunburn
- If used as directed with other sun protection measures (see Directions) decreases the risk of skin cancer and early skin aging caused by the sun

Warnings

For external use only

Do not use

on damaged or broken skin

when using this product

keep out of eyes. Rinse with water to remove.

Stop use and ask a doctor

If swallowed. get medical help or contact a Poison Control Center right away.

Keep out of reach of children.

If swallowed, get medical help or contact a Poison Control Center right away.

Directions

- Apply liberally and evenly 15 minutes before sun exposure
- Reapply at least every 2 hours
- Use a water-resistant sunscreen if swimming or sweating
- Immediately after towel drying
- At least every 2 hours
- Children under 6 months of age: Ask a doctor
- Sun Protection Measures. Spending time in the sun increases your risk of a skin cancer and early skin aging. To decrease this risk, regularly use a sunscreen with a Broad Spectrum SPF value of 15 or higher and other sun protection measures including:
- Limit time in the sun, especially from 10 a.m.-2 p.m.

Other Information

- Protect the product in this container from excessive heat and direct sun

Inactive Ingredients

WATER (AQUA), DIMETHICONE, C12-15 ALKYL BENZOATE, PROPANEDIOL, CETYL PEG/PPG-10/1 DIMETHICONE, BUTYLOCTYL SALICYLATE, ARGANIA SPINOSA KERNEL OIL, TOCOPHERYL ACETATE, SODIUM CHLORIDE, DISTEARDIMONIUM HECTORITE, NIACINAMDE, POLYGLYCERYL-4 ISOSTEARATE, HEXYL LAURATE, OLIVE OIL POLYGLYCERYL-6 ESTERS, POLYSILICONE-11, 1,2-HEXANEDIOL, CAPRYLYL GLYCOL, HYDROXYACETOPHENONE, MAGNESIUM SULFATE, PERSEA GRATISSIMA (AVOCADO) OIL, POLYGLYCERYL-6 PENAOLEATE, BUTYROSPERMUM PARKII (SHEA) BUTTER, STEARIC ACID, ALPHA-GLUCAN OLIGOSACCHARIDE, SILICA, VITIS VINIFERA (GRAPE) SEED OIL, BISABOLOL, CAFFEINE, TRIETHOXYCAPRYLYLSILANE, ALUMINA, POLYMNIA SONCHIFOLIA ROOT JUICE, POLYHYDROXYSTEARIC ACID, MALTODEXTRIN, SODIUM HYALURONATE, PHENOXYETHANOL, LACTOBACILLUS, MAY CONTAIN: IRON OXIDES (CI 77491, CI 77492, CI 77499)